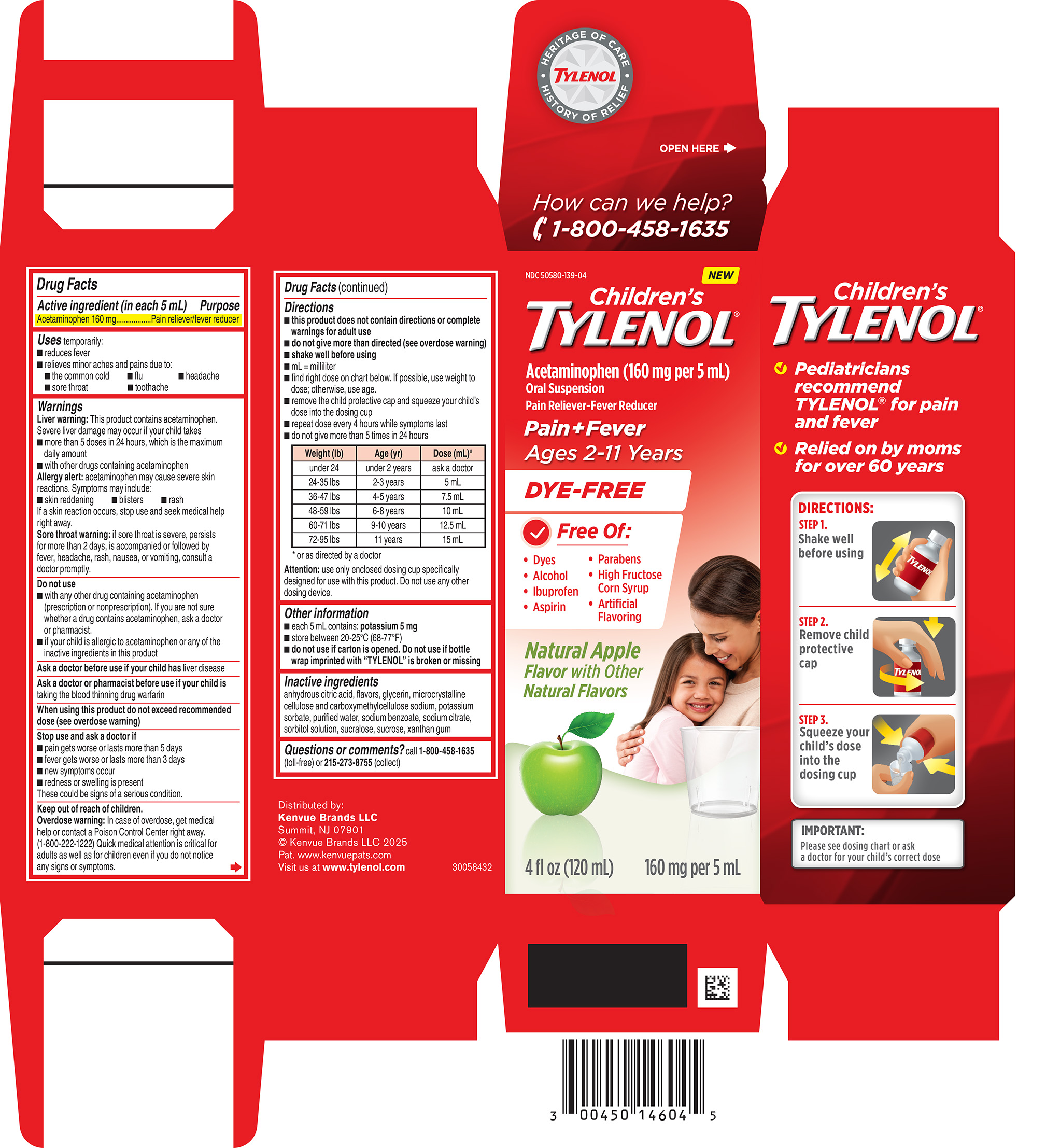 DRUG LABEL: CHILDRENS TYLENOL
NDC: 50580-139 | Form: SUSPENSION
Manufacturer: Kenvue Brands LLC
Category: otc | Type: HUMAN OTC DRUG LABEL
Date: 20250523

ACTIVE INGREDIENTS: ACETAMINOPHEN 160 mg/5 mL
INACTIVE INGREDIENTS: SODIUM CITRATE; SUCROSE; XANTHAN GUM; MICROCRYSTALLINE CELLULOSE; POTASSIUM SORBATE; SUCRALOSE; CARBOXYMETHYLCELLULOSE SODIUM, UNSPECIFIED; ANHYDROUS CITRIC ACID; GLYCERIN; SORBITOL SOLUTION; SODIUM BENZOATE; WATER

Children's Tylenol®

Drug Facts

Active ingredient

Active ingredient (in each 5 mL)

Acetaminophen 160 mg

Purpose

Pain reliever/fever reducer

Uses

Uses temporarily:

■ reduces fever

■ relieves minor aches and pains due to:
-the common cold

-flu

-headache

-sore throat

-toothache

Warnings

Liver warning

Liver warning: This product contains acetaminophen. Severe liver damage may occur if your child takes
■ more than 5 doses in 24 hours, which is the maximum daily amount
■ with other drugs containing acetaminophen

Allergy alert: acetaminophen may cause severe skin reactions. Symptoms may include:
■ skin reddening

■ blisters

■ rash

If a skin reaction occurs, stop use and seek medical help right away.

Sore throat warning: if sore throat is severe, persists for more than 2 days, is accompanied or followed by fever, headache, rash, nausea, or vomiting, consult a doctor promptly.

Do not use
■ with any other drug containing acetaminophen (prescription or nonprescription). If you are not sure whether a drug contains acetaminophen, ask a doctor or pharmacist.
■ if your child is allergic to acetaminophen or any of the inactive ingredients in this product

Ask a doctor before use if your child has liver disease

Ask a doctor or pharmacist before use if your child is taking the blood thinning drug warfarin

When using this product do not exceed recommended dose (see overdose warning)

Stop use and ask a doctor if

■ pain gets worse or lasts more than 5 days
■ fever gets worse or lasts more than 3 days
■ new symptoms occur
■ redness or swelling is present
These could be signs of a serious condition.

Keep out of reach of children.

OVERDOSAGE

Overdose warning: In case of overdose, get medical help or contact a Poison Control Center right away.
(1-800-222-1222) Quick medical attention is critical for adults as well as for children even if you do not notice any signs or symptoms.

Directions

■ this product does not contain directions or complete warnings for adult use
■ do not give more than directed (see overdose warning)
■ shake well before using
■ mL = milliliter
■ find right dose on chart below. If possible, use weight to dose; otherwise, use age.
■ remove the child protective cap and squeeze your child’s dose into the dosing cup
■ repeat dose every 4 hours while symptoms last
■ do not give more than 5 times in 24 hours

Weight (lb) | Age (yr) | Dose (mL)*
under 24 | under 2 years | ask a doctor
24-35 lbs | 2-3 years | 5 mL
36-47 lbs | 4-5 years | 7.5 mL
48-59 lbs | 6-8 years | 10 mL
60-71 lbs | 9-10 years | 12.5 mL
72-95 lbs | 11 years | 15 mL

* or as directed by a doctor

Attention: use only enclosed dosing cup specifically designed for use with this product. Do not use any other dosing device.

Other information

■ each 5 mL contains: potassium 5 mg
■ store between 20-25°C (68-77°F)
■ do not use if carton is opened. Do not use if bottle wrap imprinted with “TYLENOL” is broken or missing

Inactive ingredients

anhydrous citric acid, flavors, glycerin, microcrystalline cellulose and carboxymethylcellulose sodium, potassium sorbate, purified water, sodium benzoate, sodium citrate,sorbitol solution, sucralose, sucrose, xanthan gum

Questions or comments? call 1-800-458-1635 (toll-free) or 215-273-8755 (collect)

PACKAGE LABEL

NDC 50580-139-04

NEW

Children's TYLENOL®

Acetaminophen (160 mg per 5 mL)

Oral Suspension

Pain Reliever-Fever Reducer

Pain+Fever

Ages 2-11 Years

DYE-FREE

Free Of:

• Dyes
• Alcohol
• Ibuprofen
• Aspirin
• Parabens
• High Fructose Corn Syrup
• Artificial Flavoring
Natural Apple
Flavor with Other
Natural Flavors

4 fl oz (120 mL) 160 mg per 5 mL